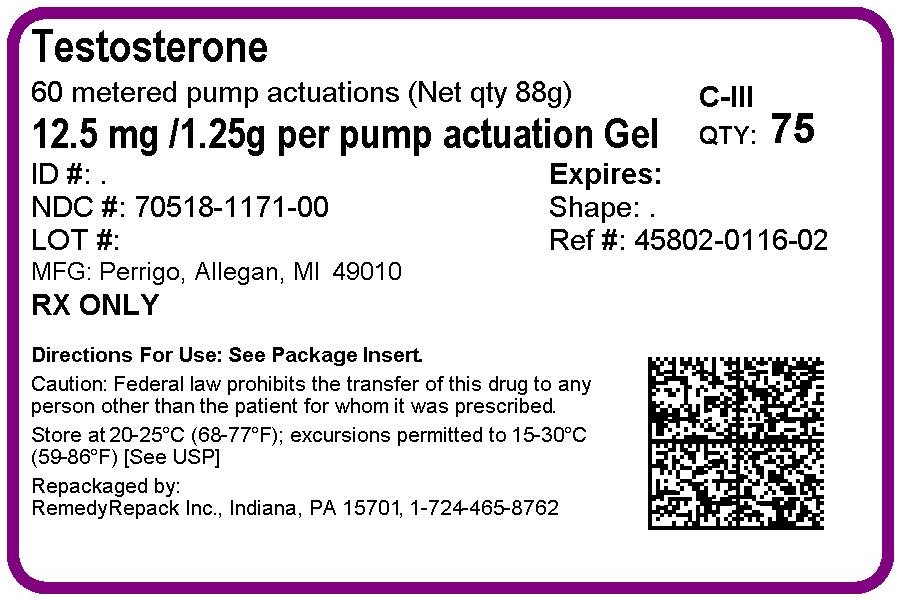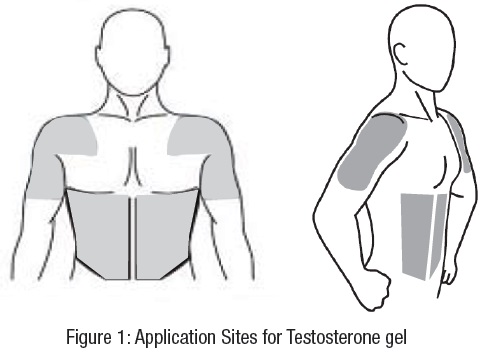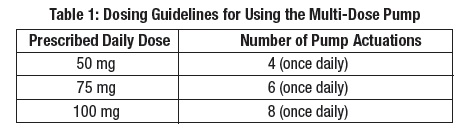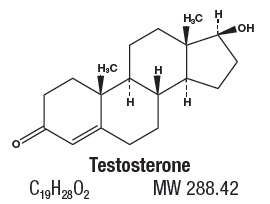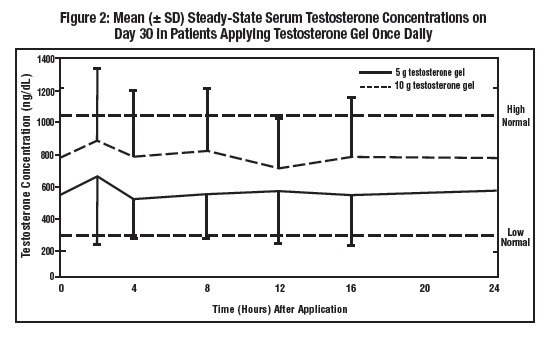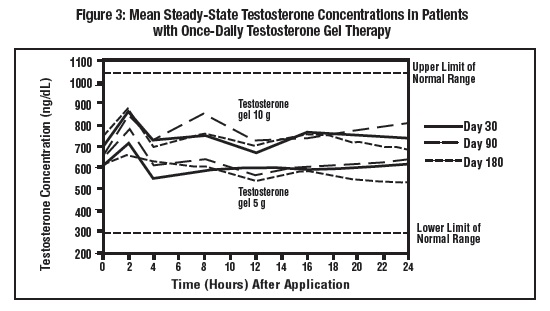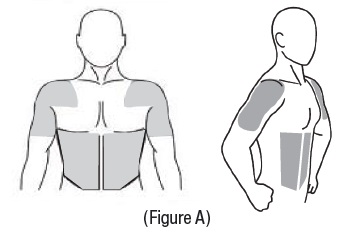 DRUG LABEL: Testosterone
NDC: 70518-1171 | Form: GEL
Manufacturer: REMEDYREPACK INC.
Category: prescription | Type: HUMAN PRESCRIPTION DRUG LABEL
Date: 20180514

ACTIVE INGREDIENTS: TESTOSTERONE 12.5 mg/1.25 g
INACTIVE INGREDIENTS: CARBOMER HOMOPOLYMER TYPE C (ALLYL PENTAERYTHRITOL CROSSLINKED); ISOSTEARIC ACID; SODIUM HYDROXIDE; WATER

HIGHLIGHTS OF PRESCRIBING INFORMATION

These highlights do not include all the information needed to use TESTOSTERONE gel safely and effectively. See full prescribing information for TESTOSTERONE gel.
TESTOSTERONE gel, for topical use, CIII
Initial U.S. Approval: 1953

WARNING: SECONDARY EXPOSURE TO TESTOSTERONE

See full prescribing information for complete boxed warning.

- Virilization has been reported in children who were secondarily exposed to testosterone gel. (5.2, 6.2)
- Children should avoid contact with unwashed or unclothed application sites in men using testosterone gel. (2.2, 5.2)
- Healthcare providers should advise patients to strictly adhere to recommended instructions for use. (2.2, 5.2, 17)

RECENT MAJOR CHANGES

Warnings and Precautions (5.6) 10/2016

1 INDICATIONS AND USAGE

Testosterone is an androgen indicated for replacement therapy in males for conditions associated with a deficiency or absence of endogenous testosterone:

- Primary Hypogonadism (Congenital or Acquired) (1)
- Hypogonadotropic Hypogonadism (Congenital or Acquired) (1)

Limitations of use:

- Safety and efficacy of testosterone gel in men with age-related hypogonadism have not been established. (1)
- Safety and efficacy of testosterone gel in males less than 18 years old have not been established. (8.4)
- Topical testosterone products may have different doses, strengths, or application instructions that may result in different systemic exposure. (1, 12.3)

2 DOSAGE AND ADMINISTRATION

- Prior to initiating testosterone gel, confirm the diagnosis of hypogonadism by ensuring that serum testosterone has been measured in the morning on at least two separate days and that these concentrations are below the normal range. (2)
- Starting dose of testosterone gel is 50 mg of testosterone (4 pump actuations, two 25 mg packets, or one 50 mg packet), applied once daily in the morning. (2.1)
- Apply to clean, dry, intact skin of shoulders and upper arms and/or abdomen. Do NOT apply testosterone gel to any other parts of the body including the genitals, chest, armpits (axillae), knees, or back. (2.2)
- Dose adjustment: Testosterone gel can be dose adjusted using 50 mg, 75 mg, or 100 mg of testosterone on the basis of total serum testosterone concentration. Additionally, serum testosterone concentration should be assessed periodically. (2.1)
- Patients should wash hands immediately with soap and water after applying testosterone gel and cover the application site(s) with clothing after the gel has dried. Wash the application site thoroughly with soap and water prior to any situation where skin-to-skin contact of the application site with another person is anticipated. (2.2)

3 DOSAGE FORMS AND STRENGTHS

Testosterone gel for topical use is available as follows:

- Metered-dose pump that delivers 12.5 mg of testosterone per actuation. (3)
- Packets containing 25 mg of testosterone. (3)
- Packets containing 50 mg of testosterone. (3)

4 CONTRAINDICATIONS

- Men with carcinoma of the breast or known or suspected prostate cancer. (4, 5.1)
- Pregnant or breast feeding women. Testosterone may cause fetal/neonatal harm. (4, 8.1, 8.3)

5 WARNINGS AND PRECAUTIONS

- Monitor patients with benign prostatic hyperplasia (BPH) for worsening of signs and symptoms of BPH (5.1).
- Avoid unintentional exposure of women or children to testosterone gel. Secondary exposure to testosterone can produce signs of virilization. Testosterone gel should be discontinued until the cause of virilization is identified. (5.2)
- Venous thromboembolism (VTE), including deep vein thrombosis (DVT) and pulmonary embolism (PE) have been reported in patients using testosterone products. Evaluate patients with signs or symptoms consistent with DVT or PE. (5.4)
- Some postmarketing studies have shown an increased risk of myocardial infarction and stroke associated with use of testosterone replacement therapy. (5.5)
- Exogenous administration of androgens may lead to azoospermia. (5.7)
- Edema, with or without congestive heart failure (CHF), may be a complication in patients with preexisting cardiac, renal, or hepatic diseases. (5.9, 6.2)
- Sleep apnea may occur in those with risk factors. (5.11)
- Monitor serum testosterone, prostatic specific antigen (PSA), hemoglobin, hematocrit, liver function tests and lipid concentrations periodically. (5.1, 5.3, 5.8, 5.12)
- Testosterone gel is flammable until dry. (5.15)

6 ADVERSE REACTIONS

Most common adverse reactions (incidence ≥ 5%) are acne, application site reactions, abnormal lab tests, and prostatic disorders. (6.1)

To report SUSPECTED ADVERSE REACTIONS, contact Perrigo at 1-866-634-9120 or FDA at 1-800-FDA-1088 or www.fda.gov/medwatch

7 DRUG INTERACTIONS

- Androgens may decrease blood glucose and therefore may decrease insulin requirements in diabetic patients. (7.1)
- Changes in anticoagulant activity may be seen with androgens. More frequent monitoring of International Normalized Ratio (“INR”) and prothrombin time is recommended. (7.2)
- Use of testosterone with adrenocorticotropic hormone (“ACTH”) or corticosteroids may result in increased fluid retention. Use with caution, particularly in patients with cardiac, renal, or hepatic disease. (7.3)

8 USE IN SPECIFIC POPULATIONS

- There are insufficient long-term safety data in geriatric patients using testosterone gel to assess the potential risks of cardiovascular disease and prostate cancer. (8.5)

FULL PRESCRIBING INFORMATION

WARNING: SECONDARY EXPOSURE TO TESTOSTERONE

- Virilization has been reported in children who were secondarily exposed to testosterone gel [ see Warnings and Precautions (5.2) and Adverse Reactions (6.2)] .
- Children should avoid contact with any unwashed or unclothed application sites in men using testosterone gel [ see Dosage and Administration (2.2), Warnings and Precautions (5.2)] .
- Healthcare providers should advise patients to strictly adhere to recommended instructions for use [ see Dosage and Administration (2.2), Warnings and Precautions (5.2) and Patient Counseling Information (17)] .

1 INDICATIONS AND USAGE

Testosterone gel is indicated for replacement therapy in adult males for conditions associated with a deficiency or absence of endogenous testosterone:

- Primary Hypogonadism (congenital or acquired) - testicular failure due to conditions such as cryptorchidism, bilateral torsion, orchitis, vanishing testis syndrome, orchiectomy, Klinefelter’s syndrome, chemotherapy, or toxic damage from alcohol or heavy metals. These men usually have low serum testosterone concentrations and gonadotropins (follicle stimulating hormone (FSH), luteinizing hormone (LH)) above the normal range.
- Hypogonadotropic hypogonadism (congenital or acquired) - gonadotropin or luteinizing hormone-releasing hormone (LHRH) deficiency or pituitary-hypothalamic injury from tumors, trauma, or radiation. These men have low testosterone serum concentrations but have gonadotropins in the normal or low range.

Limitations of use:

- Safety and efficacy of testosterone gel in men with "age-related hypogonadism" (also referred to as "late-onset hypogonadism") have not been established.
- Safety and efficacy of testosterone gel in males less than 18 years old have not been established [ see Use in Specific Populations (8.4)].
- Topical testosterone products may have different doses, strengths, or application instructions that may result in different systemic exposure. (1, 12.3)

2 DOSAGE AND ADMINISTRATION

Prior to initiating testosterone gel, confirm the diagnosis of hypogonadism by ensuring that serum testosterone concentrations have been measured in the morning on at least two separate days and that these serum testosterone concentrations are below the normal range.

2.1 Dosing and Dose Adjustment

The recommended starting dose of testosterone gel is 50 mg of testosterone (4 pump actuations, two 25 mg packets, or one 50 mg packet), applied topically once daily in the morning to the shoulders and upper arms and/or abdomen area (preferably at the same time every day).

Dose Adjustment

To ensure proper dosing, serum testosterone levels should be measured at intervals. If the serum testosterone concentration is below the normal range, the daily testosterone gel dose may be increased from 50 mg to 75 mg and from 75 mg to 100 mg for adult males as instructed by the physician (see Table 1, Dosing Information for testosterone gel). If the serum testosterone concentration exceeds the normal range, the daily testosterone gel dose may be decreased. If the serum testosterone concentration consistently exceeds the normal range at a daily dose of 50 mg, testosterone gel therapy should be discontinued. In addition, serum testosterone concentration should be assessed periodically.

2.2 Administration Instructions

Testosterone gel should be applied to clean, dry, healthy, intact skin of the right and left upper arms/shoulders and/or right and left abdomen. Area of application should be limited to the area that will be covered by the patient’s short sleeve T- shirt. Do not apply testosterone gel to any other part of the body including the genitals, chest, armpits (axillae), knees, or back. Testosterone gel should be evenly distributed between the right and left upper arms/shoulders or both sides of the abdomen.

The prescribed daily dose of testosterone gel should be applied to the right and left upper arms/shoulders and/or right/left abdomen as shown in the shaded areas in the figure below.

After applying the gel, the application site should be allowed to dry prior to dressing. Hands should be washed with soap and water after testosterone gel has been applied. Avoid fire, flames or smoking until the gel has dried since alcohol based products, including testosterone gel, are flammable.

The patient should be advised to avoid swimming or showering for at least 5 hours after the application of testosterone gel.

Multi-Dose Pump

To obtain a full first dose, it is necessary to prime the canister pump. To do so, with the canister in the upright position, slowly and fully depress the actuator three times. Safely discard the gel from the first three actuations. It is only necessary to prime the pump before the first dose. After the priming procedure, patients should completely depress the pump one time (actuation) for every 12.5 mg of testosterone required to achieve the daily prescribed dosage. The product should be delivered directly into the palm of the hand and then applied to the desired application sites. Alternatively, testosterone gel can be applied directly to the application sites.

Table 1 provides dosing information for adult males.

Packets

The entire contents should be squeezed into the palm of the hand and immediately applied to the application sites. Alternately, patients may squeeze a portion of the gel from the packet into the palm of the hand and apply to application sites. Repeat until entire contents have been applied.

Strict adherence to the following precautions is advised in order to minimize the potential for secondary exposure to testosterone from testosterone gel-treated skin:

- Children and women should avoid contact with unwashed or unclothed application site(s) of men using testosterone gel.
- Patients should wash their hands immediately with soap and water after applying testosterone gel.
- Patients should cover the application site(s) with clothing (e.g., a T-shirt) after the gel has dried.
- Prior to any situation in which skin-to-skin contact with the application site is anticipated, patients should wash the application site(s) thoroughly with soap and water to remove any testosterone residue.
- In the event that unwashed or unclothed skin to which testosterone gel has been applied comes in direct contact with the skin of another person, the general area of contact on the other person should be washed with soap and water as soon as possible.

3 DOSAGE FORMS AND STRENGTHS

Testosterone gel for topical use is available as follows:

- A metered-dose pump. Each pump actuation delivers 12.5 mg of testosterone in 1.25 g of gel.
- A unit dose packet containing 25 mg of testosterone provided in 2.5 g of gel.
- A unit dose packet containing 50 mg of testosterone provided in 5 g of gel.

4 CONTRAINDICATIONS

- Testosterone gel is contraindicated in men with carcinoma of the breast or known or suspected carcinoma of the prostate [ see Warnings and Precautions (5.1), Adverse Reactions (6.1), and Nonclinical Toxicology (13.1)].
- Testosterone gel is contraindicated in women who are or may become pregnant, or who are breastfeeding. Testosterone gel may cause fetal harm when administered to a pregnant woman. Testosterone gel may cause serious adverse reactions in nursing infants. Exposure of a female fetus or nursing infant to androgens may result in varying degrees of virilization. Pregnant women or those who may become pregnant need to be aware of the potential for transfer of testosterone from men treated with testosterone gel. If a pregnant woman is exposed to testosterone gel, she should be apprised of the potential hazard to the fetus [ see Warnings and Precautions (5.2) and Use in Specific Populations (8.1, 8.3)].

5 WARNINGS AND PRECAUTIONS

5.1 Worsening of Benign Prostatic Hyperplasia (BPH) and Potential Risk of Prostate Cancer

- Patients with BPH treated with androgens are at an increased risk for worsening of signs and symptoms of BPH. Monitor patients with BPH for worsening signs and symptoms.
- Patients treated with androgens may be at increased risk for prostate cancer. Evaluate patients for prostate cancer prior to initiating and during treatment with androgens [ see Contraindications (4), Adverse reactions (6.1) and Nonclinical Toxicology (13.1)].

5.2 Potential for Secondary Exposure to Testosterone

Cases of secondary exposure resulting in virilization of children have been reported in postmarketing surveillance. Signs and symptoms have included enlargement of the penis or clitoris, development of pubic hair, increased erections and libido, aggressive behavior, and advanced bone age. In most cases, these signs and symptoms regressed with removal of the exposure to testosterone gel. In a few cases, however, enlarged genitalia did not fully return to age-appropriate normal size, and bone age remained modestly greater than chronological age. The risk of transfer was increased in some of these cases by not adhering to precautions for the appropriate use of testosterone gel. Children and women should avoid contact with unwashed or unclothed application sites in men using testosterone gel [ see Dosage and Administration (2.2), Use in Specific Populations (8.1) and Clinical Pharmacology (12.3)].

Inappropriate changes in genital size or development of pubic hair or libido in children, or changes in body hair distribution, significant increase in acne, or other signs of virilization in adult women should be brought to the attention of a physician and the possibility of secondary exposure to testosterone gel should also be brought to the attention of a physician. Testosterone gel should be promptly discontinued until the cause of virilization has been identified.

5.3 Polycythemia

Increases in hematocrit, reflective of increases in red blood cell mass, may require lowering or discontinuation of testosterone. Check hematocrit prior to initiating treatment. It would also be appropriate to re-evaluate the hematocrit 3 to 6 months after starting treatment, and then annually. If hematocrit becomes elevated, stop therapy until hematocrit decreases to an acceptable concentration. An increase in red blood cell mass may increase the risk of thromboembolic events.

5.4 Venous Thromboembolism

There have been postmarketing reports of venous thromboembolic events, including deep vein thrombosis (DVT) and pulmonary embolism (PE), in patients using testosterone products, such as testosterone gel. Evaluate patients who report symptoms of pain, edema, warmth and erythema in the lower extremity for DVT and those who present with acute shortness of breath for PE. If a venous thromboembolic event is suspected, discontinue treatment with testosterone gel and initiate appropriate workup and management [ see Adverse Reactions (6.2)].

5.5 Cardiovascular Risk

Long term clinical safety trials have not been conducted to assess the cardiovascular outcomes of testosterone replacement therapy in men. To date, epidemiologic studies and randomized controlled trials have been inconclusive for determining the risk of major adverse cardiovascular events (MACE), such as non-fatal myocardial infarction, non-fatal stroke, and cardiovascular death, with the use of testosterone compared to non-use. Some studies, but not all, have reported an increased risk of MACE in association with use of testosterone replacement therapy in men. Patients should be informed of this possible risk when deciding whether to use or to continue to use testosterone gel.

5.6 Abuse of Testosterone and Monitoring of Serum Testosterone Concentrations

Testosterone has been subject to abuse, typically at doses higher than recommended for the approved indication and in combination with other anabolic androgenic steroids. This type of testosterone abuse can lead to serious cardiovascular and psychiatric adverse reactions [ see Drug Abuse and Dependence (9)].

If testosterone abuse is suspected, check serum testosterone concentrations to ensure they are within therapeutic range. Counsel patients concerning the serious adverse reactions associated with testosterone and anabolic androgenic steroid abuse. Conversely, consider the possibility of testosterone and anabolic androgenic steroid abuse in patients who present with serious cardiovascular or psychiatric adverse events.

5.7 Use in Women

Due to lack of controlled evaluations in women and potential virilizing effects, testosterone gel is not indicated for use in women [ see Contraindications (4) and Use in Specific Populations (8.1, 8.3)].

5.8 Potential for Adverse Effects on Spermatogenesis

At large doses of exogenous androgens, including testosterone gel; spermatogenesis may be suppressed through feedback inhibition of pituitary follicle-stimulating hormone (FSH) which could possibly lead to adverse effects on semen parameters including sperm count.

5.9 Hepatic Adverse Effects

Prolonged use of high doses of orally active 17-alpha-alkyl androgens (e.g., methyltestosterone) has been associated with serious hepatic adverse effects (peliosis hepatis, hepatic neoplasms, cholestatic hepatitis, and jaundice). Peliosis hepatis can be a life-threatening or fatal complication. Long-term therapy with intramuscular testosterone enanthate has produced multiple hepatic adenomas. Testosterone gel is not known to produce these adverse effects.

5.10 Edema

Androgens, including testosterone gel, may promote retention of sodium and water. Edema with or without congestive heart failure may be a serious complication in patients with preexisting cardiac, renal, or hepatic disease [ see Adverse Reactions (6.2)].

5.11 Gynecomastia

Gynecomastia may develop and may persist in patients being treated with androgens, including testosterone gel, for hypogonadism.

5.12 Sleep Apnea

The treatment of hypogonadal men with testosterone products may potentiate sleep apnea in some patients, especially those with risk factors such as obesity or chronic lung diseases [ see Adverse Reactions (6.2)].

5.13 Lipids

Changes in serum lipid profile may require dose adjustment or discontinuation of testosterone therapy.

5.14 Hypercalcemia

Androgens, including testosterone gel, should be used with caution in cancer patients at risk of hypercalcemia (and associated hypercalciuria). Regular monitoring of serum calcium concentrations is recommended in these patients.

5.15 Decreased Thyroxine-binding Globulin

Androgens, including testosterone gel, may decrease levels of thyroxin-binding globulin, resulting in decreased total T4 serum concentrations and increased resin uptake of T3 and T4. Free thyroid hormone concentrations remain unchanged, however, and there is no clinical evidence of thyroid dysfunction.

5.16 Flammability

Alcohol based products including testosterone gel are flammable; therefore patients should be advised to avoid fire, flame or smoking until the testosterone gel has dried.

6 ADVERSE REACTIONS

6.1 Clinical Trial Experience

Because clinical trials are conducted under widely varying conditions, adverse reaction rates observed in the clinical trials of a drug cannot be directly compared to rates in the clinical trials of another drug and may not reflect the rates observed in practice.

Clinical Trials in Hypogonadal Men

Table 2 shows the incidence of all adverse reactions with testosterone gel and reported by > 1% of patients in a 180 Day, Phase 3 study.

 | Dose of Testosterone
Adverse Reaction | 50 mg | 75 mg | 100 mg
 | N = 77 | N = 40 | N = 78
Acne | 1% | 3% | 8%
Alopecia | 1% | 0% | 1%
Application Site Reaction | 5% | 3% | 4%
Asthenia | 0% | 3% | 1%
Depression | 1% | 0% | 1%
Emotional Lability | 0% | 3% | 3%
Gynecomastia | 1% | 0% | 3%
Headache | 4% | 3% | 0%
Hypertension | 3% | 0% | 3%
Abnormal Lab Tests* | 6% | 5% | 3%
Libido Decreased | 0% | 3% | 1%
Nervousness | 0% | 3% | 1%
Pain Breast | 1% | 3% | 1%
Prostate Disorder** | 3% | 3% | 5%
Testis Disorder*** | 3% | 0% | 0%

* Abnormal lab tests occurred in nine patients with one or more of the following events reported: elevated hemoglobin or hematocrit, hyperlipidemia, elevated triglycerides, hypokalemia, decreased HDL, elevated glucose, elevated creatinine, elevated total bilirubin.

** Prostate disorders included five patients with enlarged prostate, one with BPH, and one with elevated PSA results.

*** Testis disorders were reported in two patients: one with left varicocele and one with slight sensitivity of left testis.

Other less common adverse reactions, reported in fewer than 1% of patients included: amnesia, anxiety, discolored hair, dizziness, dry skin, hirsutism, hostility, impaired urination, paresthesia, penis disorder, peripheral edema, sweating, and vasodilation.

In this 180 day clinical trial, skin reactions at the site of application were reported with testosterone gel, but none was severe enough to require treatment or discontinuation of drug.

Six patients (4%) in this trial had adverse reactions that led to discontinuation of testosterone gel. These reactions included: cerebral hemorrhage, convulsion, depression, sadness, memory loss, elevated prostate specific antigen, and hypertension. No patients on testosterone gel discontinued due to skin reactions.

In a separate uncontrolled pharmacokinetic study of 10 patients, two had adverse reactions; these were asthenia and depression in one patient and increased libido and hyperkinesia in the other.

In a 3 year, flexible dose, extension study, the incidence of all adverse reactions to testosterone gel and reported by > 1% of patients is shown in Table 3:

Table 3: Adverse Reactions to Testosterone gel in the 3 Year, Flexible Dose, Extension Study

Adverse Reaction | Percent of Subjects
 | (N = 162)
Abnormal Lab Tests+ | 9.3
Skin dry | 1.9
Application Site Reaction | 5.6
Acne | 3.1
Pruritus | 1.9
Enlarged Prostate | 11.7
Carcinoma of Prostate | 1.2
Urinary Symptoms* | 3.7
Testis Disorder** | 1.9
Gynecomastia | 2.5
Anemia | 2.5

+ Abnormal lab tests occurred in 15 patients with one or more of the following events reported: elevated AST, elevated ALT, elevated testosterone, elevated hemoglobin or hematocrit, elevated cholesterol, elevated cholesterol/LDL ratio, elevated triglycerides, elevated HDL, elevated serum creatinine.

* Urinary symptoms included nocturia, urinary hesitancy, urinary incontinence, urinary retention, urinary urgency and weak urinary stream.

** Testis disorders included three patients. There were two with a non-palpable testis and one with slight right testicular tenderness.

Two patients reported serious adverse reactions considered possibly related to treatment: deep vein thrombosis (DVT) and prostate disorder requiring a transurethral resection of the prostate (TURP).

Discontinuation for adverse reactions in this study included: two patients with application site reactions, one with kidney failure, and five with prostate disorders (including increase in serum PSA in 4 patients, and increase in PSA with prostate enlargement in a fifth patient).

Increases in Serum PSA Observed in Clinical Trials of Hypogonadal Men

During the initial 6-month study, the mean change in PSA values had a statistically significant increase of 0.26 ng/mL. Serum PSA was measured every 6 months thereafter in the 162 hypogonadal men on testosterone gel in the 3 year extension study. There was no additional statistically significant increase observed in mean PSA from 6 months through 36 months. However, there were increases in serum PSA observed in approximately 18% of individual patients. The overall mean change from baseline in serum PSA values for the entire group from month 6 to 36 was 0.11 ng/mL.

Twenty-nine patients (18%) met the per-protocol criterion for increase in serum PSA, defined as > 2X the baseline or any single serum PSA > 6 ng/mL. Most of these (25/29) met this criterion by at least doubling of their PSA from baseline. In most cases where PSA at least doubled (22/25), the maximum serum PSA value was still < 2 ng/mL. The first occurrence of a pre-specified, post-baseline increase in serum PSA was seen at or prior to Month 12 in most of the patients who met this criterion (23 of 29; 79%).

Four patients met this criterion by having a serum PSA > 6 ng/mL and in these, maximum serum PSA values were 6.2 ng/mL, 6.6 ng/mL, 6.7 ng/mL, and 10.7 ng/mL. In two of these patients, prostate cancer was detected on biopsy. The first patient’s PSA levels were 4.7 ng/mL and 6.2 ng/mL at baseline and at Month 6/Final, respectively. The second patient’s PSA levels were 4.2 ng/mL, 5.2 ng/mL, 5.8 ng/mL, and 6.6 ng/mL at baseline, Month 6, Month 12, and Final, respectively.

6.2 Postmarketing Experience

The following adverse reactions have been identified during post approval use of testosterone gel. Because the reactions are reported voluntarily from a population of uncertain size, it is not always possible to reliably estimate their frequency or establish a causal relationship to drug exposure (Table 4):

Table 4: Adverse Reactions from Postmarketing Experience of Testosterone Gel by MedDRA System Organ Class

Blood and lymphatic system disorders: | Elevated Hgb, Hct (polycythemia)
Cardiovascular disorders: | Myocardial infarction, stroke
Endocrine disorders: | Hirsutism
Gastrointestinal disorders: | Nausea
General disorders and administration site reactions: | Asthenia, edema, malaise
Genitourinary disorders: | Impaired urination
Hepatobiliary disorders: | Abnormal liver function tests (e.g., transaminases, elevated GGTP, bilirubin)
Investigations: | Elevated PSA, electrolyte changes (nitrogen, calcium, potassium, phosphorus, sodium), changes in serum lipids (hyperlipidemia, elevated triglycerides, decreased HDL), impaired glucose tolerance, fluctuating testosterone levels, weight increase
Neoplasms benign, malignant and unspecified (cysts and polyps): | Prostate cancer
Nervous system: | Headache, dizziness, sleep apnea, insomnia
Psychiatric disorders: | Depression, emotional lability, decreased libido, nervousness, hostility, amnesia, anxiety
Reproductive system and breast disorders: | Gynecomastia, mastodynia, prostatic enlargement, testicular atrophy, Oligospermia, priapism (frequent or prolonged erections)
Respiratory disorders: | Dyspnea
Skin and subcutaneous tissue disorders: | Acne, alopecia, application site reaction (pruritus, dry skin, erythema, rash, discolored hair, paresthesia), sweating
Vascular disorders: | Hypertension, vasodilation (hot flushes, venous thromboembolism)

Secondary Exposure to Testosterone in Children

Cases of secondary exposure to testosterone resulting in virilization of children have been reported in postmarket surveillance. Signs and symptoms of these reported cases have included enlargement of the clitoris (with surgical intervention) or the penis, development of pubic hair, increased erections and libido, aggressive behavior, and advanced bone age. In most cases with a reported outcome, these signs and symptoms were reported to have regressed with removal of the testosterone gel exposure. In a few cases, however, enlarged genitalia did not fully return to age appropriate normal size, and bone age remained modestly greater than chronological age. In some of the cases, direct contact with the sites of application on the skin of men using testosterone gel was reported. In at least one reported case, the reporter considered the possibility of secondary exposure from items such as the testosterone gel user’s shirts and/or other fabric, such as towels and sheets [ see Warnings and Precautions (5.2)].

7 DRUG INTERACTIONS

7.1 Insulin

Changes in insulin sensitivity or glycemic control may occur in patients treated with androgens. In diabetic patients, the metabolic effects of androgens may decrease blood glucose and, therefore, may decrease insulin requirements.

7.2 Oral Anticoagulants

Changes in anticoagulant activity may be seen with androgens, therefore more frequent monitoring of International Normalized Ratio (INR) and prothrombin time are recommended in patients taking anticoagulants, especially at the initiation and termination of androgen therapy.

7.3 Corticosteroids

The concurrent use of testosterone with adrenocorticotropic hormone (ACTH) or corticosteroids may result in increased fluid retention and requires careful monitoring particularly in patients with cardiac, renal or hepatic disease.

8 USE IN SPECIFIC POPULATIONS

8.1 Pregnancy

Pregnancy Category X [ see Contraindications (4)]:

Testosterone gel is contraindicated during pregnancy or in women who may become pregnant. Testosterone is teratogenic and may cause fetal harm. Exposure of a female fetus to androgens, such as testosterone, may result in varying degrees of virilization. If this drug is used during pregnancy, or if the patient becomes pregnant while taking this drug, the patient should be apprised of the potential hazard to a fetus.

8.3 Nursing Mothers

Although it is not known how much testosterone transfers into human milk, testosterone gel is contraindicated in nursing women because of the potential for serious adverse reactions in nursing infants. Testosterone and other androgens may adversely affect lactation. [ see Contraindications (4)].

8.4 Pediatric Use

Safety and efficacy of testosterone gel in pediatric males less than 18 years old has not been established. Improper use may result in acceleration of bone age and premature closure of epiphyses.

8.5 Geriatric Use

There have not been sufficient numbers of geriatric patients involved in controlled clinical studies utilizing testosterone gel to determine whether efficacy in those over 65 years of age differs from younger subjects. Additionally, there is insufficient long-term safety data in geriatric patients to assess the potential risks of cardiovascular disease and prostate cancer.

Geriatric patients treated with androgens may also be at risk for worsening of signs and symptoms of BPH.

8.6 Renal Impairment

No studies were conducted involving patients with renal impairment.

8.7 Hepatic Impairment

No studies were conducted in patients with hepatic impairment.

9 DRUG ABUSE AND DEPENDENCE

9.1 Controlled Substance

Testosterone gel contains testosterone, a Schedule III controlled substance in the Controlled Substances Act.

9.2 Abuse

Drug abuse is intentional non-therapeutic use of a drug, even once, for its rewarding psychological and physiological effects. Abuse and misuse of testosterone are seen in male and female adults and adolescents. Testosterone, often not obtained by prescription and not obtained through a pharmacy and typically in combination with other anabolic androgenic steroids (AAS), is abused by athletes and bodybuilders. There have been reports of misuse by men taking higher doses of legally obtained testosterone than prescribed and continuing testosterone despite adverse events or against medical advice.

Behaviors Associated with Addiction

- Continued abuse of testosterone and other anabolic steroids, leading to addiction is characterized by the following behaviors:
- Taking greater dosages than prescribed
- Continued drug use despite medical and social problems due to drug use
- Spending significant time to obtain the drug when supplies of the drug are interrupted
- Giving a higher priority to drug use than other obligations
- Having difficulty in discontinuing the drug despite desires and attempts to do so
- Experiencing withdrawal symptoms upon abrupt discontinuation of use

Abuse-Related Adverse Reactions

Serious adverse reactions, including cardiac arrest, myocardial infarction, hypertrophic cardiomyopathy, congestive heart failure, cerebrovascular accident, hepatotoxicity, and serious psychiatric manifestations, including major depression, mania, paranoia, psychosis, delusions, hallucinations, hostility and aggression, have been reported in individuals who abuse anabolic androgenic steroids.

The following adverse reactions have also been reported in men: transient ischemic attacks, convulsions, hypomania, irritability, dyslipidemias, testicular atrophy, subfertility, and infertility.

The following additional adverse reactions have been reported in women: hirsutism, virilization, deepening of voice, clitoral enlargement, breast atrophy, male-pattern baldness, and menstrual irregularities.

The following adverse reactions have been reported in male and female adolescents: premature closure of bony epiphyses with termination of growth, and precocious puberty.

Because these reactions are reported voluntarily from a population of uncertain size and may include abuse of other agents, it is not always possible to reliably estimate their frequency or establish a causal relationship to drug exposure.

9.3 Dependence

Physical dependence is characterized by withdrawal symptoms after abrupt drug discontinuation or a significant dose reduction of a drug. Individuals taking Supratherapeutic doses of testosterone may experience withdrawal symptoms lasting for weeks or months which included depressed mood, major depression, fatigue, craving, restlessness, irritability, anorexia, insomnia, decreased libido and hypogonadotropic hypogonadism. Drug dependence in individuals using approved doses of testosterone for approved indications has not been documented.

10 OVERDOSAGE

There is one report of acute overdosage with use of an approved injectable testosterone product: This subject had serum testosterone concentrations of up to 11, 400 ng/dL with a cerebrovascular accident.

Treatment of overdosage would consist of discontinuation of testosterone gel, washing the application site with soap and water, and appropriate symptomatic and supportive care.

11 DESCRIPTION

Testosterone gel is a clear, colorless hydroalcoholic gel containing testosterone.

The active pharmacologic ingredient in testosterone gel is testosterone, an androgen. Testosterone USP is a white to practically white crystalline powder chemically described as 17-beta hydroxyandrost-4-en-3-one. The structural formula is:

Inactive ingredients in testosterone gel are carbomer 980, ethanol 67.0%, isostearic acid, purified water, and sodium hydroxide. These ingredients are not pharmacologically active.

12 CLINICAL PHARMACOLOGY

12.1 Mechanism of Action

Endogenous androgens, including testosterone and dihydrotestosterone (DHT), are responsible for the normal growth and development of the male sex organs and for maintenance of secondary sex characteristics. These effects include the growth and maturation of prostate, seminal vesicles, penis and scrotum; the development of male hair distribution, such as facial, pubic, chest and axillary hair; laryngeal enlargement, vocal chord thickening, alterations in body musculature and fat distribution. Testosterone and DHT are necessary for the normal development of secondary sex characteristics. Male hypogonadism, a clinical syndrome resulting from insufficient secretion of testosterone, can present as primary hypogonadism caused by defects of the gonads, such as Klinefelter’s Syndrome or Leydig cell aplasia, while secondary hypogonadism is the failure of the hypothalamus (or pituitary) to produce sufficient gonadotropins (FSH, LH).

12.2 Pharmacodynamics

No specific pharmacodynamic studies were conducted using testosterone gel.

12.3 Pharmacokinetics

Absorption

In a single-dose, crossover clinical study conducted in 24 hypogonadal males under fasting conditions, the serum testosterone exposure (AUC0-72) and maximum testosterone concentration (Cmax) following a topical administration of 100 mg testosterone administered as 2 x 5 g testosterone gel packets (2 packets applied to the shoulder/upper arm) were bioequivalent to those following a topical administration of an approved testosterone gel product.

Testosterone gel delivers physiologic amounts of testosterone, producing circulating testosterone concentrations that approximate normal concentrations (298 to 1043 ng/dL) seen in healthy men.

Testosterone gel provides continuous transdermal delivery of testosterone for 24 hours following a single application to intact, clean, dry skin of the shoulders, upper arms and/or abdomen.

Testosterone gel is a hydroalcoholic formulation that dries quickly when applied to the skin surface. The skin serves as a reservoir for the sustained release of testosterone into the systemic circulation. Approximately 10% of the testosterone dose applied on the skin surface from testosterone gel is absorbed into systemic circulation. In a study with testosterone gel 100 mg, all patients showed an increase in serum testosterone within 30 minutes, and eight of nine patients had a serum testosterone concentration within normal range by 4 hours after the initial application. Absorption of testosterone into the blood continues for the entire 24 hour dosing interval. Serum concentrations approximate the steady-state concentration by the end of the first 24 hours and are at steady state by the second or third day of dosing.

With single daily applications of testosterone gel, follow-up measurements 30, 90, and 180 days after starting treatment have confirmed that serum testosterone concentrations are generally maintained within the eugonadal range. Figure 2 summarizes the 24-hour pharmacokinetic profiles of testosterone for hypogonadal men (< 300 ng/dL) maintained on testosterone gel 50 mg or 100 mg for 30 days. The average (± SD) daily testosterone concentration produced by 100 mg on Day 30 was 792 (± 294) ng/dL and by testosterone gel 50 mg was 566 (± 262) ng/dL.

Distribution

Circulating testosterone is primarily bound in the serum to sex hormone-binding globulin (SHBG) and albumin. Approximately 40% of testosterone in plasma is bound to SHBG, 2% remains unbound (free) and the rest is bound to albumin and other proteins.

Metabolism

Testosterone is metabolized to various 17-keto steroids through two different pathways. The major active metabolites of testosterone are estradiol and DHT.

DHT concentrations increased in parallel with testosterone concentrations during testosterone gel treatment. The mean steady-state DHT/T ratio during 180 days of testosterone gel treatment remained within normal limits and ranged from 0.23 to 0.29 (5 g/day) and from 0.27 to 0.33 (10 g/day).

Excretion

There is considerable variation in the half-life of testosterone concentration as reported in the literature, ranging from 10 to 100 minutes. About 90% of a dose of testosterone given intramuscularly is excreted in the urine as glucuronic and sulfuric acid conjugates of testosterone and its metabolites. About 6% of a dose is excreted in the feces, mostly in the unconjugated form. Inactivation of testosterone occurs primarily in the liver.

When testosterone gel treatment is discontinued after achieving steady state, serum testosterone concentrations remain in the normal range for 24 to 48 hours but return to their pretreatment concentrations by the fifth day after the last application.

Testosterone Transfer from Male Patients to Female Partners

The potential for dermal testosterone transfer following testosterone gel use was evaluated in a clinical study between males dosed with testosterone gel and their untreated female partners. Two (2) hours after application of 100 mg of testosterone from 10 g (2 x 5 g packets) of testosterone gel to upper arm and shoulder of one side by the male subjects, the couples (N = 20 couples) engaged in a 15 minute session of vigorous skin-to-skin contact so that the female partners gained maximum exposure to the testosterone gel application sites. Serum concentrations of testosterone were monitored in the female subjects for 24 hours after the transfer procedure. Under these study conditions, unprotected female partners had a mean testosterone AUC0-24 and Cmax that were more than 2 times greater than their mean baseline values. When a shirt covered the application site, study results showed a 16% and 48% increase in testosterone AUC0-24 and Cmax, respectively, compared to baseline in these females. The potential for dermal testosterone transfer following testosterone gel application on the abdomen has not been evaluated.

Effect of Hand Washing and Showering

In a separate clinical study conducted to evaluate the effect of hand washing on the residual amount of testosterone, 33 healthy male subjects received 100 mg of testosterone from 10 g (2 x 5 g packets) of testosterone gel on a hand and applied testosterone gel to the upper arm and shoulder of one side. Subjects washed their hands with liquid soap and warm tap water immediately after drug application. Then the hand was wiped with 3 ethanol dampened gauzes which were then combined together and analyzed for testosterone content. A mean (SD) of 0.40 (0.20) mg of residual testosterone (i.e., approximately 0.4% of the theoretical dose of 100 mg testosterone administered) was recovered after washing hands with liquid soap and warm tap water.

The same study also evaluated the effect of showering on the residual amount of testosterone on the application site. Subjects washed the application site by showering two hours after drug application. The application site was then wiped with 3 ethanol dampened gauzes which were then combined together and analyzed for testosterone content. A mean (SD) of 5.80 (2.77) mg of residual testosterone (i.e., approximately 5.8% of the theoretical dose of 100 mg testosterone administered) was recovered after showering.

13 NONCLINICAL TOXICOLOGY

13.1 Carcinogenesis, Mutagenesis, Impairment of Fertility

Carcinogenicity

Testosterone has been tested by subcutaneous injection and implantation in mice and rats. In mice, the implant induced cervical-uterine tumors, which metastasized in some cases. There is suggestive evidence that injection of testosterone into some strains of female mice increases their susceptibility to hepatoma. Testosterone is also known to increase the number of tumors and decrease the degree of differentiation of chemically induced carcinomas of the liver in rats.

Mutagenesis

Testosterone was negative in the in vitro Ames and in the in vivo mouse micronucleus assays.

Impairment of Fertility

The administration of exogenous testosterone has been reported to suppress spermatogenesis in the rat, dog and non-human primates, which was reversible on cessation of the treatment.

14 CLINICAL STUDIES

14.1 Clinical Trials in Adult Hypogonadal Males

Testosterone gel was evaluated in a multi-center, randomized, parallel-group, active-controlled, 180 day trial in 227 hypogonadal men. The study was conducted in 2 phases. During the Initial Treatment Period (Days 1 to 90), 73 patients were randomized to testosterone gel 50 mg daily, 78 patients to testosterone gel 100 mg daily, and 76 patients to a non-scrotal testosterone transdermal system. The study was double-blind for dose of testosterone gel but open-label for active control. Patients who were originally randomized to testosterone gel and who had single-sample serum testosterone levels above or below the normal range on Day 60 were titrated to 75 mg daily on Day 91. During the Extended Treatment Period (Days 91 to 180), 51 patients continued on testosterone gel 50 mg daily, 52 patients continued on testosterone gel 100 mg daily, 41 patients continued on a non-scrotal testosterone transdermal system (5 mg daily), and 40 patients received testosterone gel 75 mg daily. Upon completion of the initial study, 163 enrolled and 162 patients received treatment in an open-label extension study of testosterone gel for an additional period of up to 3 years.

Mean peak, trough and average serum testosterone concentrations within the normal range (298 to 1043 ng/dL) were achieved on the first day of treatment with doses of 50 mg and 100 mg of testosterone gel. In patients continuing on testosterone gel 50 mg and 100 mg, these mean testosterone levels were maintained within the normal range for the 180-day duration of the original study.

Figure 3 summarizes the 24 hour pharmacokinetic profiles of testosterone administered as testosterone gel for 30, 90 and 180 days. Testosterone concentrations were maintained as long as the patient continued to properly apply the prescribed testosterone gel treatment.

Table 5 summarizes the mean testosterone concentrations on Treatment Day 180 for patients receiving 50 mg, 75 mg, or 100 mg, of testosterone. The 75 mg dose produced mean concentrations intermediate to those produced by 50 mg and 100 mg of testosterone.

Table 5: Mean (± SD) Steady-State Serum Testosterone Concentrations During Therapy (Day 180)

 | 50 mg; N = 44 | 75 mg; N = 37 | 100 mg; N = 48
Cavg | 555 ± 225 | 601 ± 309 | 713 ± 209
Cmax | 830 ± 347 | 901 ± 471 | 1083 ± 434
Cmin | 371 ± 165 | 406 ± 220 | 485 ± 156

Of 129 hypogonadal men who were appropriately titrated with testosterone gel and who had sufficient data for analysis, 87% achieved an average serum testosterone level within the normal range on Treatment Day 180.

In patients treated with testosterone gel, there were no observed differences in the average daily serum testosterone concentrations at steady-state based on age, cause of hypogonadism, or body mass index.

14.2 Skin Irritation Study

Testosterone gel was evaluated in a randomized, five-treatment, single-center, controlled, within-subject comparison study with healthy subjects using a cumulative irritation patch test design. Thirty-three (33) subjects completed the study involving testosterone gel, a comparator control product, vehicle, and positive and negative controls. All five treatments were applied to the skin separately with an occlusive patch. Each subject received a set of 5 patches, once daily for 21 consecutive days. Evaluation of dermal reactions at the application sites were assessed every day at the time of removal of each patch using an established ordinal (6-point) scoring system. Testosterone gel showed no evidence of significant irritation and was statistically significantly less irritating than the positive control (P<0.001).

14.3 Skin Sensitization Study

Testosterone gel was evaluated in a randomized, five-treatment, single-center, controlled, within-subject study to evaluate the sensitizing potential on healthy volunteers, using a Repeat Insult Patch Test design. Two hundred three (203) subjects completed the study involving Testosterone Gel, a comparator control product, vehicle, and positive and negative controls. All five treatments were applied to the skin separately with an occlusive patch. Each subject received a set of 5 patches, every 48-72 hours for 21 consecutive days. Evaluation of dermal reactions at the application sites were assessed clinically every day at the time of removal of each patch using an established ordinal (6-point) scoring system. Observations at the naïve site during challenge and the pattern of reactivity during induction provided bases for an interpretation of contact sensitizations. Under these conditions there was no evidence of sensitization to testosterone gel, In the cumulative irritancy analysis, testosterone gel was statistically significantly less irritating than the positive control (P<0.001).

16 HOW SUPPLIED/STORAGE AND HANDLING

16.1 How Supplied

Testosterone gel is supplied in non-aerosol, metered-dose pumps that deliver 12.5 mg of testosterone per complete pump actuation. The pumps are composed of plastic and stainless steel and an LDPE/aluminum foil inner liner encased in rigid plastic with a polypropylene cap. Each 88 g metered-dose Pump is capable of dispensing 75 g of gel or 60 metered pump actuations; each pump actuation dispenses 1.25 g of gel containing 12.5 mg of testosterone.

NDC Number | Package Size
45802- 116-02 | 2 x 75 g pumps (each pump dispenses 60 metered pump actuations with each pump actuation containing 12.5 mg of testosterone in 1.25 g of gel)

Testosterone gel is also supplied in unit-dose aluminum foil packets in cartons of 30.

Each packet of 2.5 g or 5 g gel contains 25 mg or 50 mg testosterone, respectively.

NDC Number | Package Size
45802- 116-65 | 30 packets (25 mg of testosterone in 2.5 g of gel per packet)
45802- 116-39 | 30 packets (50 mg of testosterone in 5 g of gel per packet)

16.2 Storage and Handling

Store at 20-25°C (68-77°F). [See USP Controlled Room Temperature.]

16.3 Disposal

Used testosterone gel pumps or used testosterone gel packets should be discarded in household trash in a manner that prevents accidental application or ingestion by children or pets.

17 PATIENT COUNSELING INFORMATION

See FDA-Approved patient labeling (Medication Guide)

Patients should be informed of the following:

17.1 Use in Men with Known or Suspected Prostate or Breast Cancer

Men with known or suspected prostate or breast cancer should not use testosterone gel [ see Contraindications (4) and Warnings and Precautions (5.1)].

17.2 Potential for Secondary Exposure to Testosterone and Steps to Prevent Secondary Exposure

Secondary exposure to testosterone in children and women can occur with the use of testosterone gel in men. Cases of secondary exposure to testosterone have been reported in children.

Physicians should advise patients of the reported signs and symptoms of secondary exposure which may include the following:

- In children; unexpected sexual development including inappropriate enlargement of the penis or clitoris, premature development of pubic hair, increased erections, and aggressive behavior
- In women; changes in hair distribution, increase in acne, or other signs of testosterone effects
- The possibility of secondary exposure to testosterone gel should be brought to the attention of a healthcare provider
- Testosterone gel should be promptly discontinued until the cause of virilization is identified
- Strict adherence to the following precautions is advised to minimize the potential for secondary exposure to testosterone from testosterone gel in men.
- Children and women should avoid contact with unwashed or unclothed application site(s) of men using testosterone gel
- Patients using testosterone gel should apply the product as directed and strictly adhere to the following:
  - Wash hands with soap and water after application
  - Cover the application site(s) with clothing after the gel has dried
  - Wash the application site(s) thoroughly with soap and water prior to any situation where skin-to-skin contact of the application site with another person is anticipated
  - In the event that unwashed or unclothed skin to which testosterone gel has been applied comes in contact with the skin of another person, the general area of contact on the other person should be washed with soap and water as soon as possible [ see Dosage and Administration (2.2), Warnings and Precautions (5.2) and Clinical Pharmacology (12.3)].

17.3 Potential Adverse Reactions with Androgens

Patients should be informed that treatment with androgens may lead to adverse reactions which include:

- Changes in urinary habits such as increased urination at night, trouble starting your urine stream, passing urine many times during the day, having an urge that you have to go to the bathroom right away, having a urine accident, being unable to pass urine and weak urine flow.
- Breathing disturbances, including those associated with sleep, or excessive daytime sleepiness.
- Too frequent or persistent erections of the penis.
- Nausea, vomiting, changes in skin color, or ankle swelling.

17.4 Patients Should Be Advised of the Following Instructions for Use:

- Read the Medication Guide before starting testosterone gel therapy and reread it each time the prescription is renewed
- Testosterone gel should be applied and used appropriately to maximize the benefits and to minimize the risk of secondary exposure in children and women
- Keep testosterone gel out of the reach of children
- Testosterone gel is an alcohol based product and is flammable; therefore avoid fire, flame or smoking until the gel has dried
- It is important to adhere to all recommended monitoring
- Report any changes in their state of health, such as changes in urinary habits, breathing, sleep, and mood
- Testosterone gel is prescribed to meet the patient’s specific needs; therefore, the patient should never share testosterone gel with anyone.
- Wait 5 hours before showering or swimming. This will ensure that the greatest amount of testosterone gel is absorbed into their system.

Made in Israel

Manufactured by Perrigo Israel Pharmaceuticals Ltd., Yeruham, Israel

Distributed by Perrigo, Allegan, MI 49010

Rev 10-16

: 1C200 RC J5

MEDICATION GUIDE

testosterone gel

Testosterone (tes-TOS-te-rone gel) CIII

Read this Medication Guide that comes with testosterone gel before you start using it and each time you get a refill. There may be new information. This Medication Guide does not take the place of talking to your healthcare provider about your medical condition or your treatment.

What is the most important information I should know about testosterone gel?

1. Early signs and symptoms of puberty have happened in young children who were accidentally exposed to testosterone through contact with men using testosterone gel.

Signs and symptoms of early puberty in a child may include:

- enlarged penis or clitoris
- early development of pubic hair
- increased erections or sex drive
- aggressive behavior

Testosterone gel can transfer from your body to others.

2. Women and children should avoid contact with the unwashed or unclothed area where testosterone gel has been applied to your skin.

Stop using testosterone gel and call your healthcare provider right away if you see any signs and symptoms in a child or a woman that may have occurred through accidental exposure to testosterone gel.

Signs and symptoms of exposure to testosterone gel in children may include:

- enlarged penis or clitoris
- early development of pubic hair
- increased erections or sex drive
- aggressive behavior

Signs and symptoms of exposure to testosterone gel in women may include:

- changes in body hair
- a large increase in acne

To lower the risk of transfer of testosterone gel from your body to others, you should follow these important instructions:

- Apply testosterone gel only to areas that will be covered by a short sleeve T-shirt. These areas are your shoulders and upper arms, or stomach area (abdomen), or shoulders, upper arms and stomach area.
- Wash your hands right away with soap and water after applying testosterone gel.
- After the gel has dried, cover the application area with clothing. Keep the area covered until you have washed the application area well or have showered.
- If you expect to have skin-to-skin contact with another person, first wash the application area well with soap and water.
- If a woman or child makes contact with the testosterone gel application area, that area on the woman or child should be washed well with soap and water right away.

What is testosterone gel?

Testosterone gel is a prescription medicine that contains testosterone. Testosterone gel is used to treat adult males who have low or no testosterone due to certain medical conditions.

Your healthcare provider will test your blood before you start and while you are using testosterone gel.

It is not known if testosterone gel is safe or effective to treat men who have low testosterone due to aging.

It is not known if testosterone gel is safe or effective in children younger than 18 years old. Improper use of testosterone gel may affect bone growth in children.

Testosterone gel is a controlled substance (CIII) because it contains testosterone that can be a target for people who abuse prescription medicines. Keep your testosterone gel in a safe place to protect it. Never give your testosterone gel to anyone else, even if they have the same symptoms you have. Selling or giving away this medicine may harm others and is against the law.

Testosterone gel is not meant for use in women.

Who should not use testosterone gel?

Do not use testosterone gel if you:

- have breast cancer
- have or might have prostate cancer
- are pregnant or may become pregnant or breast-feeding. Testosterone gel may harm your unborn or breast-feeding baby.
- Women who are pregnant or who may become pregnant should avoid contact with the area of skin where testosterone gel has been applied.

Talk to your healthcare provider before taking this medicine if you have any of the above conditions.

What should I tell my healthcare provider before using testosterone gel?

Before you use testosterone gel, tell your healthcare provider if you:

- have breast cancer
- have or might have prostate cancer
- have urinary problems due to an enlarged prostate
- have heart problems
- have liver or kidney problems
- have problems breathing while you sleep (sleep apnea)
- have any other medical conditions

Tell your healthcare provider about all the medicines you take, including prescription and non-prescription medicines, vitamins, and herbal supplements.

Using testosterone gel with certain other medicines can affect each other.

Especially, tell your healthcare provider if you take:

- insulin
- corticosteroids
- medicines that decrease blood clotting

Know the medicines you take. Ask your healthcare provider or pharmacist for a list of these medicines, if you are not sure. Keep a list of them and show it to your healthcare provider and pharmacist when you get a new medicine.

How should I use testosterone gel?

- It is important that you apply testosterone gel exactly as your healthcare provider tells you to.
- Your healthcare provider will tell you how much testosterone gel to apply and when to apply it.
- Your healthcare provider may change your testosterone gel dose. Do not change your testosterone gel dose without talking to your healthcare provider.
- Testosterone gel is to be applied to the area of your shoulders, upper arms, or abdomen that will be covered by a short sleeve t-shirt. Do not apply testosterone gel to any other parts of your body such as your penis, scrotum, chest, armpits (axillae), knees, or back.
- Apply testosterone gel at the same time each morning. Testosterone gel should be applied after showering or bathing.
- Wash your hands right away with soap and water after applying testosterone gel.
- Avoid showering, swimming, or bathing for at least 5 hours after you apply testosterone gel.
- Testosterone gel is flammable until dry. Let testosterone gel dry before smoking or going near an open flame.
- Let the application areas dry before putting on a t-shirt.

Applying testosterone gel:

Testosterone gel comes in a pump or in packets.

- Before applying testosterone gel, make sure that your shoulders, upper arms, and abdomen are clean, dry, and there is no broken skin.
- The application sites for testosterone gel are the shoulders, upper arms, or abdomen that will be covered by a short sleeve t-shirt (See Figure A).

If you are using the testosterone gel pump:

- Before using a new bottle of testosterone gel for the first time, you will need to prime the pump. To prime the testosterone gel pump, slowly push the pump all the way down 3 times.
- Do not use any testosterone gel that came out while priming. Wash it down the sink to avoid accidental exposure to others. Your testosterone gel pump is now ready to use.
- Remove the cap from the pump. Then, position the nozzle over the palm of your hand and slowly push the pump all the way down. Apply testosterone gel to the application site. You may also apply testosterone gel directly to the application site.
- Wash your hands with soap and water right away.
- Your healthcare provider will tell you the number of times to press the pump for each dose.

If you are using testosterone gel packets:

- Tear open the packet completely at the dotted line. Squeeze from the bottom of the packet to the top.
- Squeeze all of the testosterone gel out of the packet into the palm of your hand. Apply testosterone gel to the application site. You may also apply testosterone gel from the packet directly to the application site.
- Testosterone gel should be applied right away.
- Wash your hands with soap and water right away.

What are the possible side effects of testosterone gel?

Testosterone gel can cause serious side effects including:

- See “What is the most important information I should know about testosterone gel?”
- If you already have enlargement of your prostate gland your signs and symptoms can get worse while using testosterone gel. This can include:
  - increased urination at night
  - trouble starting your urine stream
  - having to pass urine many times during the day
  - having an urge that you have to go to the bathroom right away
  - having a urine accident
  - being unable to pass urine or weak urine flow
- Possible increased risk of prostate cancer. Your healthcare provider should check you for prostate cancer or any other prostate problems before you start and while you use testosterone gel.
- Blood clots in the legs or lungs. Signs and symptoms of a blood clot in your leg can include leg pain, swelling or redness. Signs and symptoms of a blood clot in your lungs can include difficulty breathing or chest pain.
- Possible increased risk of heart attack or stroke.
- In large doses testosterone gel may lower your sperm count.
- Swelling of your ankles, feet, or body, with or without heart failure.
- Enlarged or painful breasts.
- Have problems breathing while you sleep (sleep apnea).

Call your healthcare provider right away if you have any of the serious side effects listed above.

The most common side effects of testosterone gel include:

- acne
- skin irritation where testosterone gel is applied
- lab test changes
- increased prostate specific antigen (a test used to screen for prostate cancer)

Other side effects include more erections than are normal for you or erections that last a long time.

Tell your healthcare provider if you have any side effect that bothers you or that does not go away.

These are not all the possible side effects of testosterone gel. For more information, ask your healthcare provider or pharmacist.

Call your doctor for medical advice about side effects. You may report side effects to FDA at 1-800-FDA-1088.

How should I store testosterone gel?

- Store testosterone gel between 68°F to 77°F (20°C to 25°C).
- Safely throw away used testosterone gel in household trash. Be careful to prevent accidental exposure of children or pets.
- Keep testosterone gel away from fire.

Keep testosterone gel and all medicines out of the reach of children.

General information about the safe and effective use of testosterone gel.

Medicines are sometimes prescribed for purposes other than those listed in a Medication Guide. Do not use testosterone gel for a condition for which it was not prescribed. Do not give testosterone gel to other people, even if they have the same symptoms you have. It may harm them.

This Medication Guide summarizes the most important information about testosterone gel. If you would like more information, talk to your healthcare provider. You can ask your pharmacist or healthcare provider for information about testosterone gel that is written for health professionals.

For more information, go to www.perrigo.com or call 1-866-634-9120

What are the ingredients in testosterone gel?

Active ingredient: testosterone

Inactive ingredients: carbomer 980, ethyl alcohol 67.0%, isostearic acid, purified water and sodium hydroxide.

This Medication Guide has been approved by the U.S. Food and Drug Administration.

Made in Israel

Manufactured By Perrigo

Yeruham, Israel

Distributed By

Perrigo®

Allegan, MI 49010

www.perrigo.com

Rev 05-15

: 1C200 RC J5

PACKAGE LABEL

DRUG: Testosterone

GENERIC: Testosterone

DOSAGE: GEL

ADMINSTRATION: TOPICAL

NDC: 70518-1171-0

PACKAGING: 88 g in 1 BOTTLE, PUMP

OUTER PACKAGING: 2 in 1 CARTON

ACTIVE INGREDIENT(S):

- TESTOSTERONE 12.5mg in 1.25g

INACTIVE INGREDIENT(S):

- CARBOMER HOMOPOLYMER TYPE C (ALLYL PENTAERYTHRITOL CROSSLINKED)
- SODIUM HYDROXIDE
- ISOSTEARIC ACID
- WATER